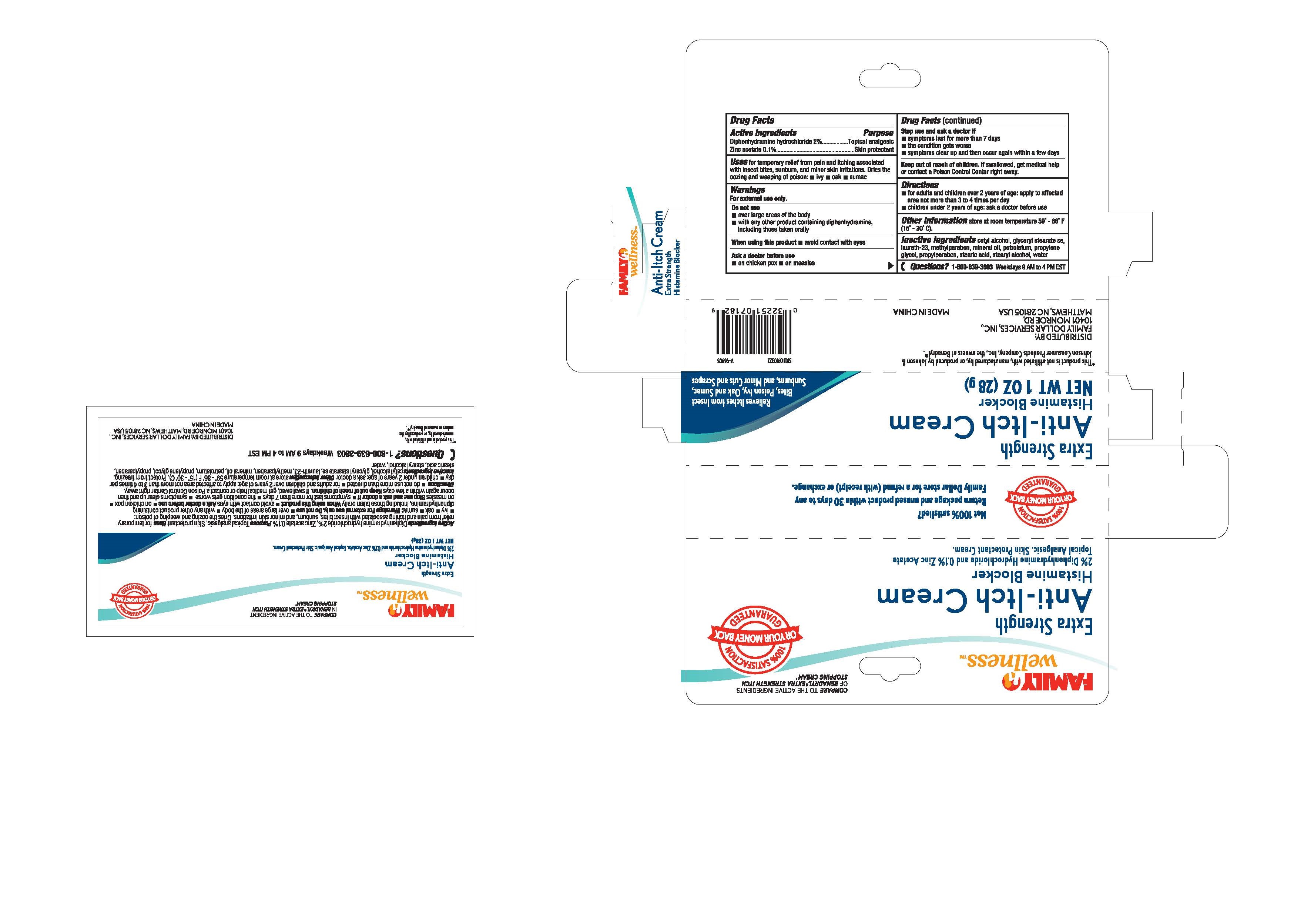 DRUG LABEL: Family Wellness
NDC: 69571-005 | Form: CREAM
Manufacturer: FRONT PHARMACEUTICAL PLC
Category: otc | Type: HUMAN OTC DRUG LABEL
Date: 20231026

ACTIVE INGREDIENTS: DIPHENHYDRAMINE HYDROCHLORIDE 2 g/100 g; ZINC ACETATE 0.1 g/100 g
INACTIVE INGREDIENTS: CETYL ALCOHOL; GLYCERYL STEARATE SE; LAURETH-23; METHYLPARABEN; MINERAL OIL; PETROLATUM; PROPYLENE GLYCOL; PROPYLPARABEN; STEARIC ACID; STEARYL ALCOHOL; WATER

Family Wellness Anti-Itch Cream, 28g

Active Ingredients

Diphenhydramine hydrochloride 2%

Zinc acetate 0.1%

Purpose

Topical analgesic

Skin protectant

INDICATIONS AND USAGE

for temprary relief from pain and itching associated Uses

with insect bites , sunburn and mior skin irritations. Dries the

oozing and weeping of poison: •ivy •oak •sumac

Warnings

. For external use only

Do not use

•avoid contact with eyes When using this product

Ask a doctor before use

•on chicken pox •on measles

Stop use and ask a doctor if

- over large areas of the body
- with any other product containing diphenhydramine including those taken orally

- symptoms last for more than 7 days
- the condition gets worse
- symptoms clear up and then occur again within a few days

KEEP OUT OF REACH OF CHILDREN

. If swallowed, get medical help Keep out of reach of children

or contact a Poison Control Center right away.

Directions

•for adults and children over 2 years of age: apply to affected

area not more than 3 to 4 times daily

•children under 2 years of age: ask a doctor before use

OTHER SAFETY INFORMATION

store at room temperature 59° - 86° F Other information

(15° - 30° C).

cetyl alcohol, glyceryl stearate se, Inactive ingredients

laureth-23, methylparaben, mineral oil, petrolatum, propylene

glycol, propylparaben, stearic acid, stearic alcohol, water

QUESTIONS

1-800-639-3803 Weekdays 9 AM to 4 PM EST Questions?